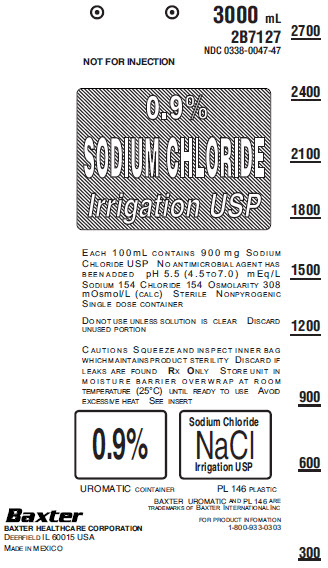 DRUG LABEL: Sodium Chloride
NDC: 0338-0047 | Form: IRRIGANT
Manufacturer: Baxter Healthcare Company
Category: prescription | Type: HUMAN PRESCRIPTION DRUG LABEL
Date: 20170504

ACTIVE INGREDIENTS: SODIUM CHLORIDE 900 mg/100 mL
INACTIVE INGREDIENTS: Water

Directions for Use of Flexible Plastic Irrigation Containers

If desired, warm in overwrap to near body temperature in a water bath or oven heated to not more than 45°C.

Parenteral drug products should be inspected visually for particulate matter and discoloration prior to administration whenever solution and container permit.

DIRECTIONS FOR USE

Tear overwrap down side at slit and remove solution container. Visually inspect the container. If the outlet port protector is damaged, detached, or not present, discard container as solution path sterility may be impaired. Some opacity of the plastic due to moisture absorption during the sterilization process may be observed. This is normal and does not affect the solution quality or safety. The opacity will diminish gradually. Check for minute leaks by squeezing bag firmly. If leaks are found, discard solution as sterility may be impaired.

Use Aseptic Technique.

1. Suspend container using hanger hole.
2. Remove plastic protector from outlet port at bottom of container.
3. Attach irrigation set. Refer to complete directions accompanying set.

Exposure of pharmaceutical products to heat should be minimized. Avoid excessive heat. It is recommended the product be stored at room temperature (25°C): brief exposure up to 40°C does not adversely affect the product.

Baxter Healthcare Corporation
Deerfield, IL 60015 USA

Printed in Mexico

©Copyright 1980, 1984, 1989, Baxter Healthcare Corporation.
All rights reserved.

Rev. May 2017

88-80-31-833

PRINCIPAL DISPLAY PANEL - PACKAGING LABELING

3000 mL
2B77127
NDC 0338-0047-47

NOT FOR INJECTION

0.9%
SODIUM CHLORIDE
Irrigation USP

Each 100 mL contains 900 mg Sodium
Chloride USP No antimicrobial agent has
been added pH 5.5 (4.5 to 7.0) mEq/L
Sodium 154 Chloride 154 Osmolarity 308
mOsmol/L (calc) Sterile Nonpyrogenic
Single dose container

Do not use unless solution is clear Discard
unused portion

Cautions Squeeze and inspect inner bag
which maintains product sterility Discard if
leaks are found Rx Only Store unit in
moisture barrier overwrap at room
temperature (25°C) until ready to use Avoid
excessive heat See insert

0.9%

Sodium Chloride
NaCl
Irrigation USP

UROMATIC container

PL 146 plastic

BAXTER UROMATIC and PL 146 are
trademarks of Baxter International Inc

For product information
1-800-933-0303

Baxter Logo
Baxter Healthcare Corporation
Deerfield, IL 60015 USA

Made in Mexico

2700

2400

2100

1800

1500

1200

900

600

300